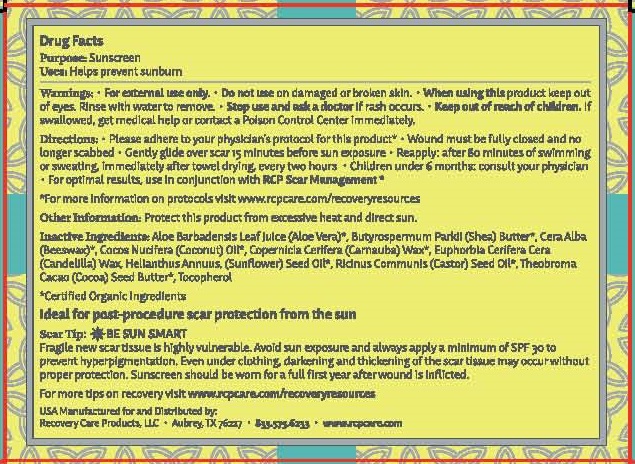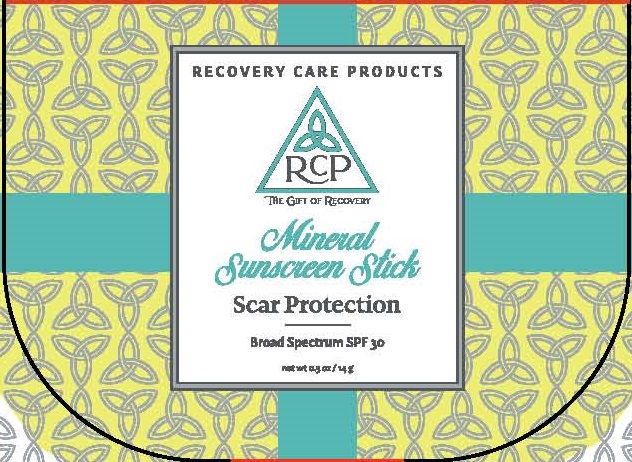 DRUG LABEL: MINERAL SUNSCREEN

NDC: 72525-003 | Form: STICK
Manufacturer: RECOVERY CARE PRODUCTS, LLC
Category: otc | Type: HUMAN OTC DRUG LABEL
Date: 20220121

ACTIVE INGREDIENTS: ZINC OXIDE 20 g/100 g
INACTIVE INGREDIENTS: ALOE VERA LEAF; SHEA BUTTER; YELLOW WAX; COCONUT OIL; CARNAUBA WAX; CANDELILLA WAX; SUNFLOWER OIL; CASTOR OIL; COCOA BUTTER; TOCOPHEROL

RECOVERY CARE PRODUCTS - MINERAL SUNSCREEN SPF 30 (72525-003)

ACTIVE INGREDIENT:

ZINC OXIDE 20%

PURPOSE:

SUNSCREEN

USES:

HELPS PREVENT SUNBURN

WARNINGS:

- FOR EXTERNAL USE ONLY.
- DO NOT USE ON DAMAGED OR BROKEN SKIN.
- WHEN USING THIS PRODUCT KEEP OUT OF EYES. RINSE WITH WATER TO REMOVE.
- STOP USE AND ASK A DOCTOR IF RASH OCCURS.

- KEEP OUT OF REACH OF CHILDREN. IF SWALLOWED, GET MEDICAL HELP OR CONTACT A POISON CONTROL CENTER IMMEDIATELY.

DIRECTIONS:

- PLEASE ADHERE TO YOUR PHYSICIAN'S PROTOCOL FOR THIS PRODUCT*
- WOULD MUST BE FULLY CLOSED AND NO LONGER SCABBED
- GENTLY GLIDE OVER SCAR 15 MINUTES PRIOR TO SUN EXPOSURE
- REAPPLY: AFTER 80 MINUTES OF SWIMMING OR SWEATING, IMMEDIATELY AFTER TOWEL DRYING, EVERY TWO HOURS
- CHILDREN UNDER 6 MONTHS: CONSULT YOUR PHYSICIAN
- FOR OPTIMAL RESULTS, USE IN CONJUNCTION WITH RCP SCAR MANAGEMENT*

*FOR MORE INFORMATION ON PROTOCOLS VISIT WWW.RCPCARE.COM/RECOVERYRESOURCES

OTHER INFORMATION:

PROTECT THIS PRODUCT FROM EXCESSIVE HEAT AND DIRECT SUN.

INACTIVE INGREDIENTS:

ALOE BARBADENSIS LEAF JUICE (ALOE VERA)*, BUTYROSPERMUM PARKII (SHEA) BUTTER*, CERA ALBA (BEESWAX)*, COCOS NUCIFERA (COCONUT) OIL*, COPERNICIA CERIFERA (CARNAUBA) WAX*, EUPHORBIA CERIFERA CERA (CANDELILLA) WAX, HELIANTHUS ANNUUS (SUNFLOWER) SEED OIL*, RICINUS COMMUNIS (CASTOR) SEED OIL*, THEOBROMA CACAO (COCOA) SEED BUTTER*, TOCOPHEROL

*CERTIFIED ORGANIC INGREDIENTS